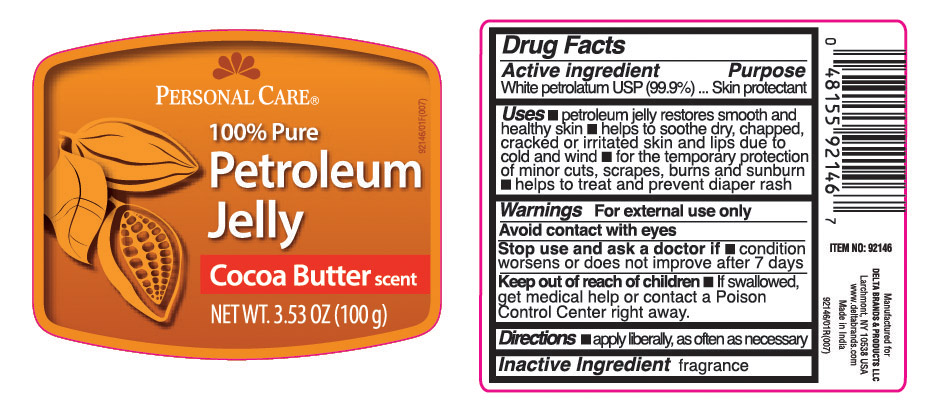 DRUG LABEL: Personal CARE
NDC: 72133-506 | Form: OINTMENT
Manufacturer: Delta Brands & Products LLC
Category: otc | Type: HUMAN OTC DRUG LABEL
Date: 20180423

ACTIVE INGREDIENTS: PETROLATUM 99.9 g/100 g

Drug Facts

Active ingredient

White petrolatum USP (99.9%)

Purpose

Skin protectant

Uses

■ petroleum jelly restores smooth and healthy skin ■ helps to soothe dry, chapped, cracked or irritated skin and lips due to cold and wind ■ for the temporary protection of minor cuts, scrapes, burns and sunburn ■ helps to treat and prevent diaper rash

Warnings

For external use only

Avoid contact with eyes

Stop use and ask a doctor if

■ condition worsens or does not improve after 7 days

Keep out of reach of children

■ if swallowed get medical help or contact a Poison Control Center right away.

Directions

■ apply liberally, as often as necessary

Inactive Ingredients

fragrance